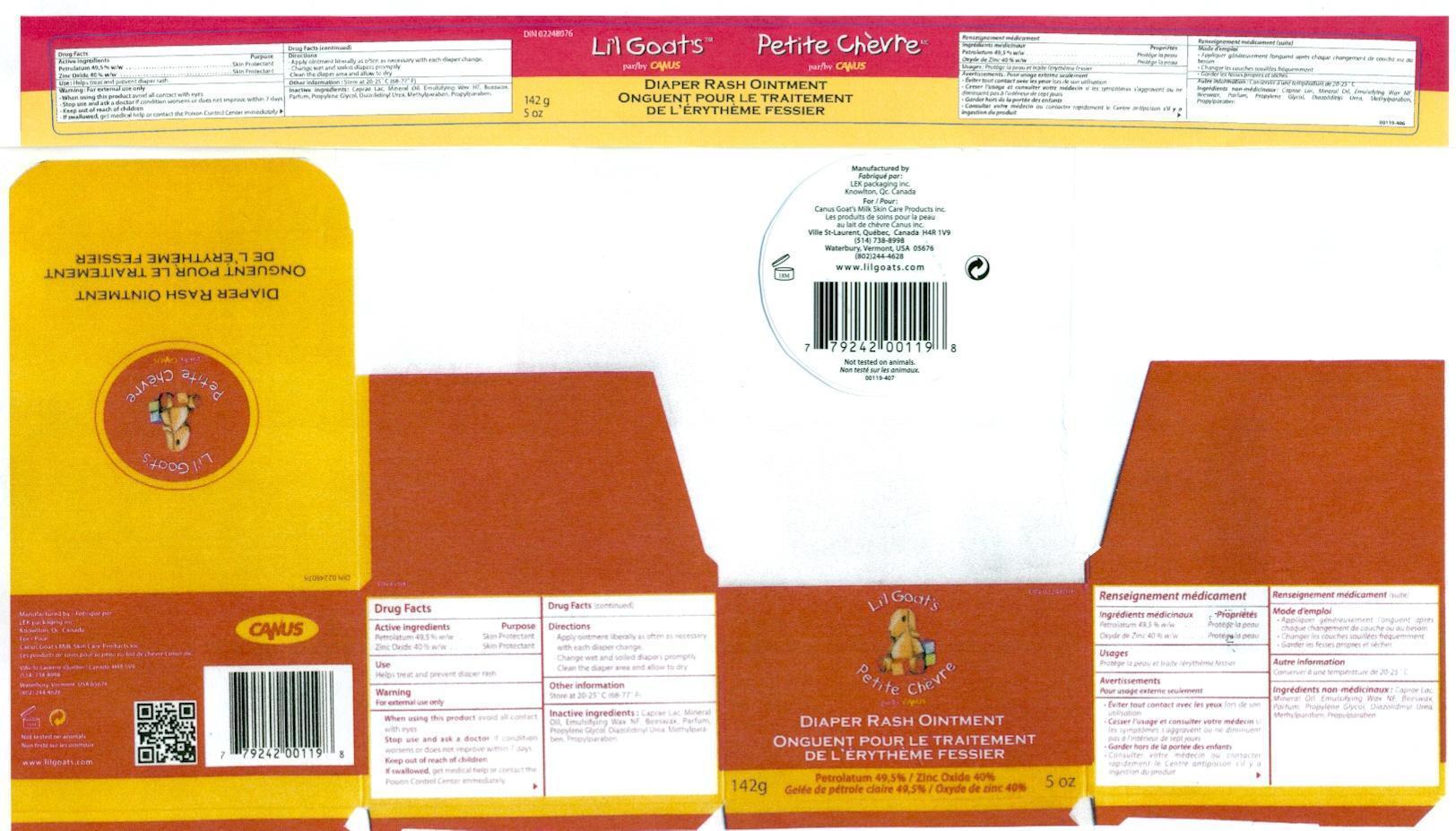 DRUG LABEL: Lil Goats Zinc Oxide
NDC: 10100-119 | Form: CREAM
Manufacturer: Canus Vermont LLC
Category: otc | Type: HUMAN OTC DRUG LABEL
Date: 20130206

ACTIVE INGREDIENTS: ZINC OXIDE 40 g/142 g; PETROLATUM 49.5 g/142 g
INACTIVE INGREDIENTS: MINERAL OIL 2.5 g/142 g; GOAT MILK 5 g/142 g

Lil Goats Diaper Rash Ointment

Active Ingredients:

Petrolatum

Zinc Oxide

Purpose:

Skin Protectant.

Use:

Helps treat and prevent diaper rash

WARNING:

For external use only.

When using this product,

avoid all contact with eyes.

Stop use and ask a doctor:

if condition worsens or does not improve within 7 days.

Keep out of reach of children.

If swallowed:

get medical help or contact the Poison Control Center immediately.

Directions:

Apply oitment literally as often as necessary with each diaper change.

Change wet and soiled diapers promptly.

Clean the diaper area and allow to dry.

Store:

at 20-25°C (68-77°F)

Inactive Ingredients:

Caprae Lac, Meneral Oil, Emulsifying Wax NF, Beeswax, Parfum, Propylene Glycol, Dizolidinyl Urea, Methylparaben, Propylparaben.

Manufactured by:

LEK Packaging Inc.

Knowlton, Qc, Canada

For:

Canus Goats Milk Skin Care Products Inc.

Les produits de soins pour la peru au lait de chèvre Canus inc.

Questions:

Tel: (514)-738-8998, Ville St-Laurent, Qc, Canada

Tel: (802) 244-4628, Waterbury USA, 05676

Other information:

Not tested on animals.

142g/5oz

wrap label and Carton